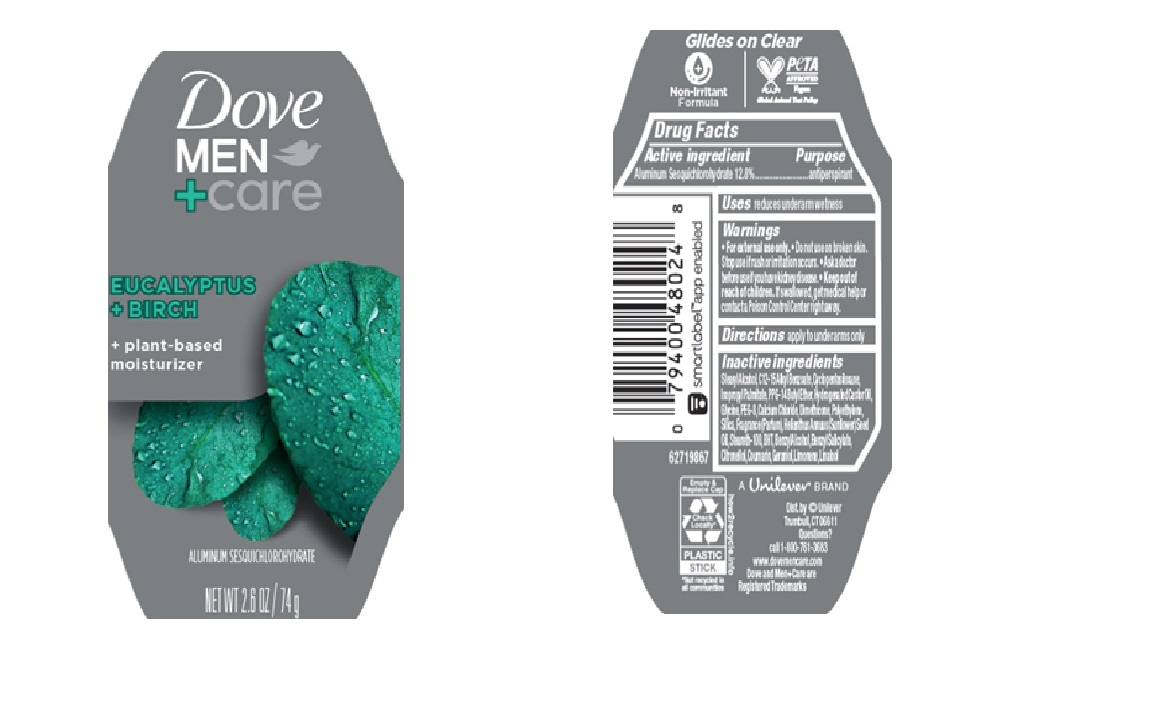 DRUG LABEL: Dove
NDC: 64942-2357 | Form: STICK
Manufacturer: Conopco d/b/a/ Unilever
Category: otc | Type: HUMAN OTC DRUG LABEL
Date: 20250331

ACTIVE INGREDIENTS: ALUMINUM SESQUICHLOROHYDRATE 12.8 g/100 g
INACTIVE INGREDIENTS: DIMETHICONE; BENZYL ALCOHOL; COUMARIN; CYCLOPENTASILOXANE; CALCIUM CHLORIDE; POLYETHYLENE; GERANIOL; LIMONENE, (+)-; BENZYL SALICYLATE; CITRONELLOL; C12-15 ALKYL BENZOATE; STEARYL ALCOHOL; HYDROGENATED CASTOR OIL; SILICA; BHT; PEG-8; HELIANTHUS ANNUUS (SUNFLOWER) SEED OIL; STEARETH-100; ISOPROPYL PALMITATE; PPG-14 BUTYL ETHER; LINALOOL, (+/-)-; GLYCINE

Dove Men + Care Eucalyptus + Birch 72H Antiperspirant

DESCRIPTION

Dove Men + Care Eucalyptus + Birch 72H Antiperspirant

ACTIVE INGREDIENT

Aluminum Sesquichlorohydrate (12.8)

PURPOSE

antiperspirant

INDICATIONS AND USAGE

reduces underarm wetness

WARNINGS

For external use only.

Do not use on broken skin.

Ask a doctor before use if you have kidney disease.

Stop use if rash or irritation occurs.

INACTIVE INGREDIENT

Stearyl Alcohol,C12 -15 Alkyl Benzoate,Cyclopentasiloxane, Isopropyl Palmitate,PPG -14 Butyl Ether,Hydrogenated Castor Oil, Glycine,PEG -8,Calcium Chloride,Dimethicone,Polyethylene, Silica,Fragrance (Parfum),Helianthus Annuus (Sunflower) Seed Oil,Steareth-100, BHT, Benzyl Alcohol, Benzyl Salicylate, Citronellol,Coumarin,Geraniol,Limonene,Linalool

Keep out of reach of children. If swallowed, get medical help or contact a Poison Control Center right away.

DOSAGE AND ADMINISTRATION

apply to underarms only

QUESTIONS

call 1-800-761-3683